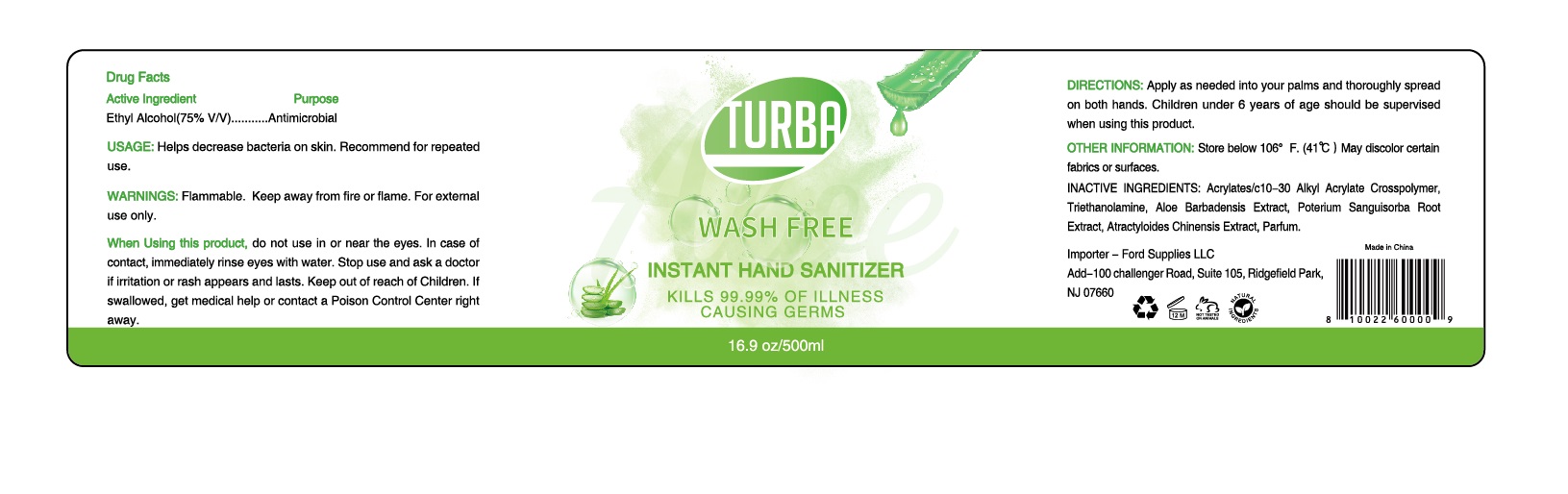 DRUG LABEL: TURBA WASH FREE INSTANT HAND SANITIZER
NDC: 75137-006 | Form: GEL
Manufacturer: Guangzhou JiuTai Bio-technology Co., Ltd.
Category: otc | Type: HUMAN OTC DRUG LABEL
Date: 20201203

ACTIVE INGREDIENTS: ALCOHOL 75 mL/100 mL
INACTIVE INGREDIENTS: ATRACTYLODES LANCEA WHOLE; SANGUISORBA MINOR ROOT; TROLAMINE; ALOE VERA LEAF; CARBOMER INTERPOLYMER TYPE A (ALLYL SUCROSE CROSSLINKED)

75137-006
Change 75137-005 to 75137-006
TURBA WASH FREE INSTANT HAND SANITIZER

Active Ingredient

Ethyl Alcohol(75%V/V)

Purpose

Antimicrobial

USAGE

Helps decrease bacteria on skin.

Recommend for repeated use.

WARNINGS

Flammable.Keep away from fire or flame.For external use only.

When Using this product

do not use in or near the eyes.In case of contact, immediately rinse eyes with water.Stop use and ask a

doctor if irritation or rash appears and lasts. Keep out of reach of Children.If swallowed,get medical help

or contact a Poison Control Center right away.

DIRECTIONS

Apply as needed into your palms and thoroughly spread on both hands.

Children under 6 years of age should be supervised when using this product.

OTHER INFORMATION

Store below 106°F.(41℃)

May discolor certain fabrics or surfaces.

INACTIVE INGREDIENTS

Acrylates/c10-30 alkyl Acrylate Crosspolymer, Triethanolamine, aloe Barbadensis Extract, Poterium Sanguisorba Root Extract, Atractyloides Chinensis Extract, Parfum